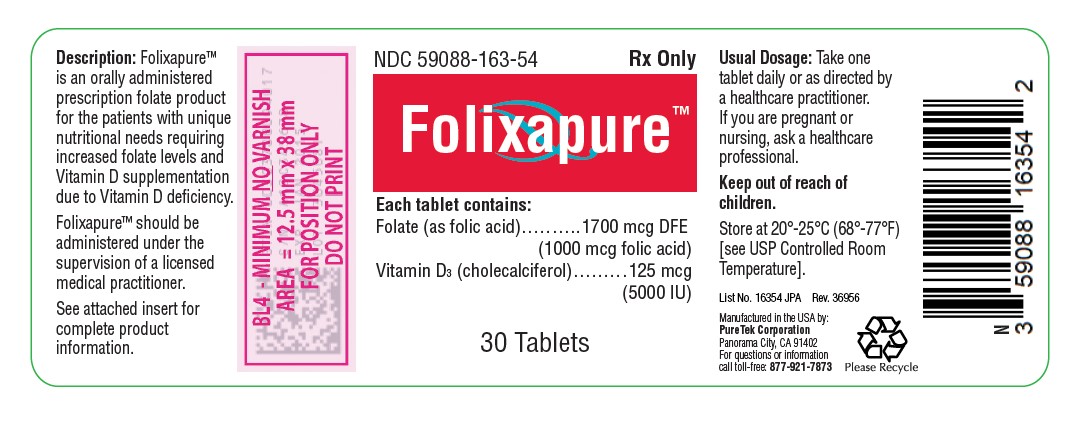 DRUG LABEL: Folixapure
NDC: 59088-163 | Form: TABLET
Manufacturer: PureTek Corporation
Category: prescription | Type: HUMAN PRESCRIPTION DRUG LABEL
Date: 20230111

ACTIVE INGREDIENTS: FOLIC ACID 1 mg/1 1; VITAMIN D 125 ug/1 1
INACTIVE INGREDIENTS: CELLULOSE, MICROCRYSTALLINE; LACTOSE MONOHYDRATE; SODIUM STARCH GLYCOLATE TYPE A CORN; MAGNESIUM STEARATE; STEARIC ACID

Folixapure Tablets
[Folate (as folic acid) 1700 mcg DFE (1000 mcg folic acid), VitaminD3 (cholecalciferol) 125 mcg (5000IU)]
Rx Only

DESCRIPTION

Folixapure™ is an orally administered prescription folate product for the dietary management of patients with unique nutritional needs requiring increased folate levels and Vitamin D supplementation due to Vitamin D deficiency.

Folixapure™ should be administered under the supervision of a licensed medical practitioner.

Each tablet contains:
Folic Acid ..........................................................................1700 mcg DFE

(1000 mcg folic acid)
Vitamin D3 (cholecalciferol) ......................................125 mcg

5000 IU

Each tablet contains the following inactive ingredients: lactose monohydrate, microcrystalline cellulose, sodium starch glycolate, stearic acid, magnesium stearate.

INDICATIONS AND DOSAGE

Folixapure™ is indicated for dietary management of patients with unique nutritional needs requiring increased folate levels and Vitamin D supplementation.

Folixapure™ can be taken by women of childbearing age, pregnant women, and lactating and nonlactating mothers.

CLINICAL PHARMACOLOGY

The in vivo synthesis of the major biologically active metabolites of vitamin D occurs in two steps. The first hydroxylation of ergocalciferol takes place in the liver (to 25-hydroxyvitamin D) and the second in the kidneys (to 1,25-dihydroxyvitamin D). Vitamin D metabolites promote the active absorption of calcium and phosphorus by the small intestine, thus elevating serum calcium and phosphate levels sufficiently to permit bone mineralization. Vitamin D metabolites also mobilize calcium and phosphate from bone and probably increase the reabsorption of calcium and perhaps also of phosphate by the renal tubules.

There is a time lag of 10 to 24 hours between the administration of vitamin D and the initiation of its action in the body due to the necessity of synthesis of the active metabolites in the liver and kidneys. Parathyroid hormone is responsible for the regulation of this metabolism in the kidneys.

CONTRAINDICATIONS

This product is contraindicated in patients with a known hypersensitivity to any of the ingredients. Folixapure™ is contraindicated in patients with hypercalcemia, malabsorption syndrome, abnormal sensitivity to the toxic effects of vitamin D, and hypervitaminosis D.

WARNINGS AND PRECAUTIONS

Tell your doctor if you have: kidney problems, thyroid disease. This medication should be used as directed during pregnancy or while breast-feeding. Consult your doctor about the risks and benefits.

Folic acid alone is improper therapy in the treatment of pernicious anemia and other megaloblastic anemias where vitamin B12 is deficient. Folic acid in doses above 0.1 mg daily may obscure pernicious anemia in that hematologic remission can occur while neurological manifestations progress.

ADVERSE REACTIONS

Allergic sensitization has been reported following both oral and parenteral administration of folic acid.

You should call your doctor for medical advice about serious adverse events. To report adverse side effects or to obtain product information, contact PureTek Corporation, at 1-877-921-7873.

DOSAGE AND ADMINISTRATION

Take one tablet daily or as directed by a healthcare practitioner.

HOW SUPPLIED

Folixapure™ Tablets are supplied as round, light yellow tablets with one side scored, the other side plain and dispensed in child-resistant bottles of 30 tablets (NDC 59088-163-54*).

* This product is a prescription-folate with or without other dietary ingredients that – due to increased folate levels (AUG 2 1973 FR 20750), requires an Rx on the label because of increased risk associated with masking of B12 deficiency (pernicious anemia). Based on our assessment of the risk of obscuring pernicious anemia, this product requires licensed medical supervision, an Rx status, and a National Drug Code (NDC) or similarly-formatted product code, as required by pedigree reporting requirements and supply-chain control as well as in some cases, for insurance-reimbursement applications.

All prescriptions using this product shall be pursuant to state statutes as applicable. This is not an Orange Book product. This product may be administered only under a physician’s supervision. There are no implied or explicit claims on therapeutic equivalence

STORAGE

KEEP OUT OF THE REACH OF CHILDREN.

Store at 20°-25°C (68°-77°F); excursions permitted to 15°-30°C (59°-86°F) [see USP Controlled Room Temperature].

Protect from heat, light and moisture.

Tamper Evident: Do not use if seal is broken or missing

Manufactured in the USA by:
PureTek Corporation
Panorama City, CA 91402
For questions or information
call toll-free: 877-921-7873

PACKAGE LABEL / PRINCIPAL DISPLAY PANEL

Manufactured in the USA by:
PureTek Corporation
Panorama City, CA 91402
For questions or information
call toll-free: 877-921-7873

List No. 16354 JPA Rev. 36956